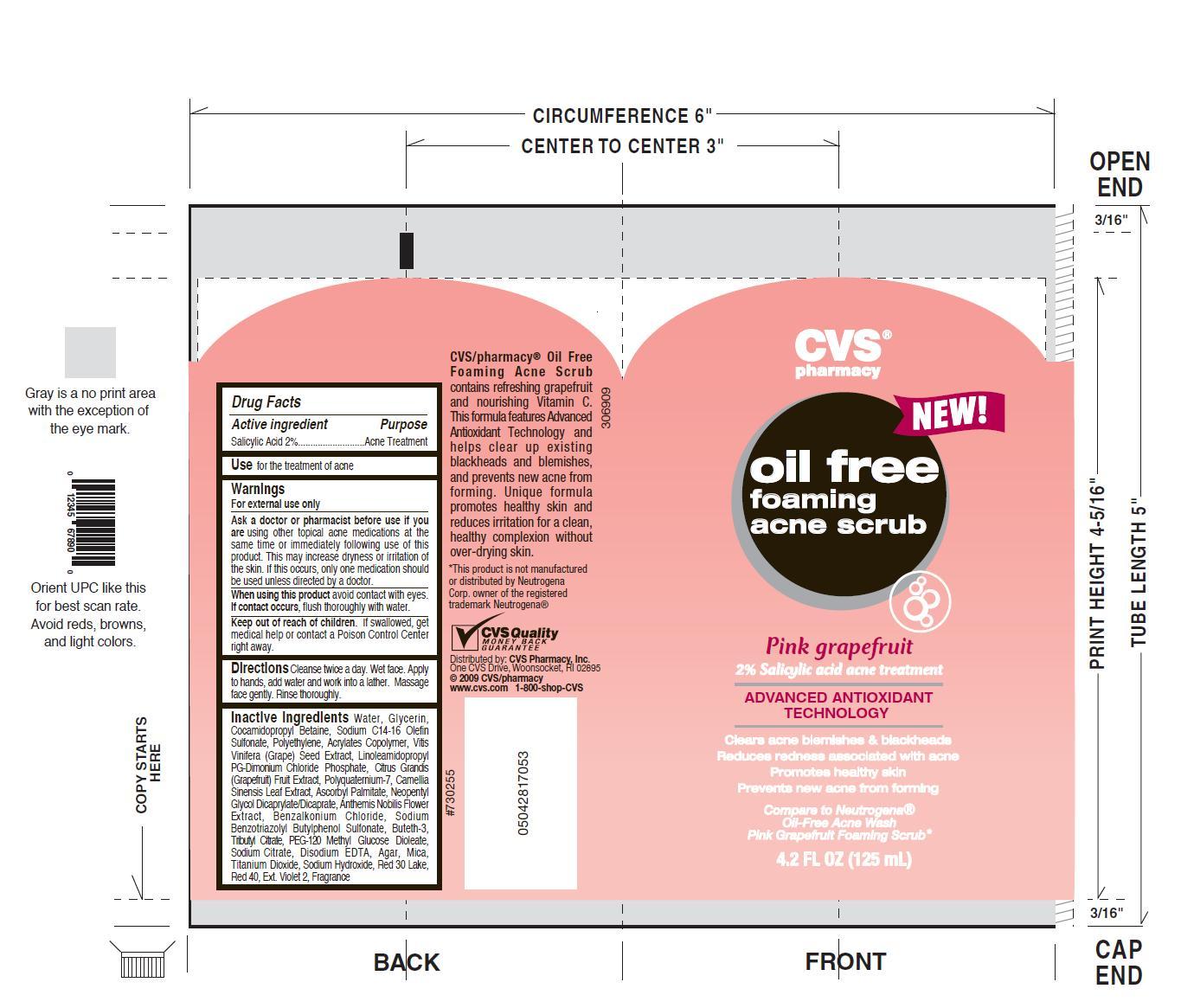 DRUG LABEL: Oil Free Acne Scrub
NDC: 57501-953 | Form: LIQUID
Manufacturer: Apex International Mfg
Category: otc | Type: HUMAN OTC DRUG LABEL
Date: 20100708

ACTIVE INGREDIENTS: Salicylic Acid 2.5 g/125 g
INACTIVE INGREDIENTS: Water; Glycerin; Cocamidopropyl Betaine; Sodium C14-16 Olefin Sulfonate; Ethylene; Acrylic Acid

Drug Facts

Drug Facts
Active Ingredient Salicylic Acid 2%
Purpose Acne Treatment
Use for the treatment of acne

Warnings

For external use only

Ask a doctor or pharmacist before use if you are using other topical acne medications at the same time or immediately following use of this product. This may increase dryness or irritation of the skin. If this occurs, only one medication should be used unless directed by a doctor.

When using this product avoid contact with eyes. If contact occurs, flush thoroughly with water.

Keep out of reach of children. If swallowed, get medical help or contact a Poison Control Center right away.

PATIENT COUNSELING INFORMATION

Directions Cleanse twice a day. Wet face. Apply to hands, add water and work into a lather. Massage face gently. Rinse thoroughly.

INACTIVE INGREDIENT

Inactive Ingredients Water, Glycerin, Cocamidopropyl Betaine, Sodium C14-16 Olefin Sulfonate, Polyethylene, Acrylates Copolymer, Vistis Vinifera (Grape) Seed Extract, Linoleamidopropyl PG-Dimonium Chloride Phosphate, Citrus Grandis (Grapefruit) Fruit Extract, Polyquaternium-7, Camellia Sinensis Leaf Extract, Ascorbyl Palmitate, Neopentyl Glycol Dicaprylate/Dicaprate, Anthemis Nobilis Flower Extract, Benzalkonium Chloride, Sodium Benzotriazolyl Butylphenol Sulfonate, Buteth-3, Tributyl Citrate, PEG-12 Methyl Glucose Dioleate, Sodium Citrate, Disodium EDTA, Agar, Mica, Titanium Dioxide, Sodium Hydroxide, Red 30 Lake, Red 40, Ext. Violet 2, Fragrance